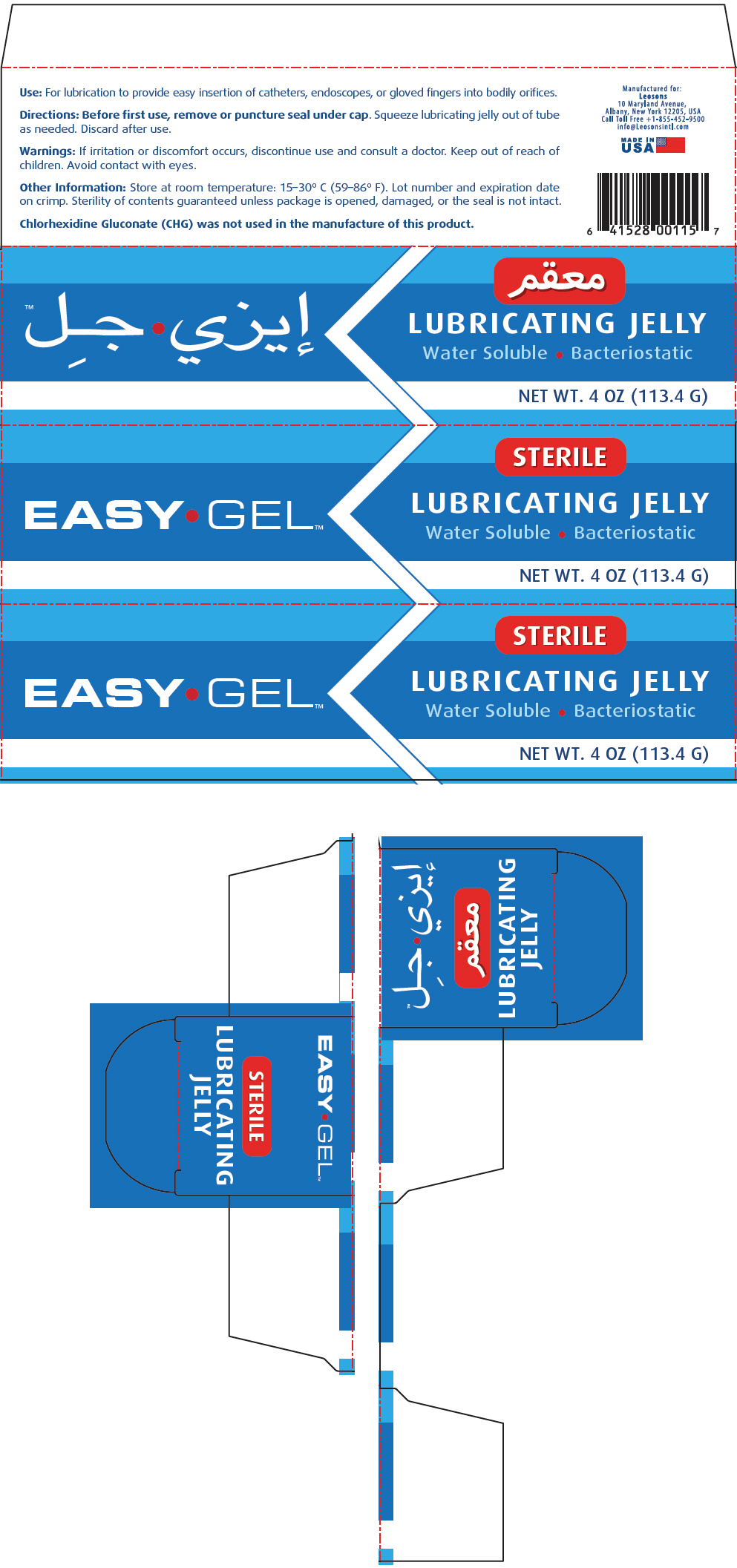 DRUG LABEL: Easy Gel
NDC: 69626-0011 | Form: GEL
Manufacturer: Leosons Overseas Corp
Category: other | Type: MEDICAL DEVICE
Date: 20161214

EASY GEL™

Use

For lubrication to provide easy insertion of catheters, endoscopes, or gloved fingers into bodily orifices.

Directions

Before first use, remove or puncture seal under cap. Squeeze lubricating jelly out of tube as needed. Discard after use.

Warnings

If irritation or discomfort occurs, discontinue use and consult a doctor. Keep out of reach of children. Avoid contact with eyes.

Other Information

Store at room temperature: 15–30º C (59–86º F). Lot number and expiration date on crimp. Sterility of contents guaranteed unless package is opened, damaged, or the seal is not intact.

Chlorhexidine Gluconate (CHG) was not used in the manufacture of this product.

PRINCIPAL DISPLAY PANEL - 113.4 G Tube Box

EASY•GEL™

STERILE

LUBRICATING JELLY

Water Soluble • Bacteriostatic

NET WT. 4 OZ (113.4 G)